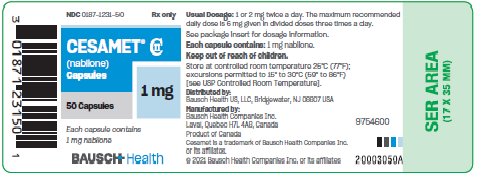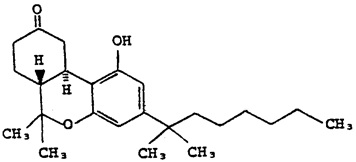 DRUG LABEL: Cesamet
NDC: 0187-1231 | Form: CAPSULE
Manufacturer: Bausch Health US LLC
Category: prescription | Type: HUMAN PRESCRIPTION DRUG LABEL
Date: 20210119
DEA Schedule: CII

ACTIVE INGREDIENTS: NABILONE 1 mg/1 1
INACTIVE INGREDIENTS: FD&C BLUE NO. 2; FERRIC OXIDE RED; GELATIN, UNSPECIFIED; TITANIUM DIOXIDE

Cesamet® (nabilone) Capsules CII

DESCRIPTION

Cesamet® (nabilone) is a synthetic cannabinoid for oral administration. Nabilone as a raw material occurs as a white to off-white polymorphic crystalline powder. In aqueous media, the solubility of nabilone is less than 0.5 mg/L, with pH values ranging from 1.2 to 7.0.

Chemically, nabilone is similar to the active ingredient found in naturally occurring Cannabis sativa L. [Marijuana; delta-9-tetrahydrocannabinol (delta-9-THC)]. Nabilone is (±)-trans-3-(1,1-dimethylheptyl)-6,6a,7,8,10,10a-hexahydro-1-hydroxy-6-6-dimethyl-9H-dibenzo[b,d]pyran-9-one and has the empirical formula C24H36O3. It has a molecular weight of 372.55. The structural formula is as follows:

Each 1 mg Cesamet capsule contains 1 mg of nabilone and the following inactive ingredients: povidone and corn starch. The capsule shells contain the following inactive ingredients: FD&C Blue No. 2 (indigo carmine), red iron oxide, gelatin, and titanium dioxide.

CLINICAL PHARMACOLOGY

Pharmacodynamics

Cesamet (nabilone) is an orally active synthetic cannabinoid which, like other cannabinoids, has complex effects on the central nervous system (CNS). It has been suggested that the antiemetic effect of nabilone is caused by interaction with the cannabinoid receptor system, i.e., the CB (1) receptor, which has been discovered in neural tissues.

Nontherapeutic Effects: Cesamet, a synthetic cannabinoid, has the potential to be abused and to produce psychological dependence. Cesamet has complex effects on the central nervous system. Its effects on the mental state (i.e., “inner mental life”) are similar to those of cannabis. Subjects given Cesamet may experience changes in mood (euphoria, detachment, depression, anxiety, panic, paranoia), decrements in cognitive performance and memory, a decreased ability to control drives and impulses, and alterations in the experience of reality (e.g., distortions in the perception of objects and the sense of time, hallucinations). These phenomena appear to be more common when larger doses of Cesamet are administered; however, a full-blown picture of psychosis (psychotic organic brain syndrome) may occur in patients receiving doses within the lower portion of the therapeutic range.

Data on the chronic use of Cesamet are not available; experience with cannabis suggests that chronic use of cannabinoids may be associated with a variety of untoward effects on motivation, cognition, judgment, as well as other mental status changes. Whether these phenomena reflect the underlying character of individuals chronically abusing cannabis or are a result of the use of cannabis is not known.

The simultaneous use of Cesamet and alcohol or barbiturates may produce additive depressive effects on central nervous system function. Possible changes in mood and other adverse behavioral effects may occur in patients receiving Cesamet. Patients should remain under supervision of a responsible adult while using Cesamet.

Cesamet has central nervous system activity. It produces relaxation, drowsiness, and euphoria in the recommended dosage range. Tolerance to these effects develops rapidly and is readily reversible.

In addition to effects on the mental state, Cesamet has several systemic actions; most prominent are dry mouth and hypotension. Cesamet has been observed to elevate supine and standing heart rates and to cause supine and orthostatic hypotension. In clinical studies, oral administration of 2 mg of Cesamet did produce some decrease in airway resistance in normal controls but had no effect in patients with asthma. No other nontherapeutic effects of clinical significance due to Cesamet have been reported.

Pharmacokinetics

Absorption and Distribution: Cesamet (nabilone) appears to be completely absorbed from the human gastrointestinal tract when administered orally. Following oral administration of a 2 mg dose of radiolabeled nabilone, peak plasma concentrations of approximately 2 ng/mL nabilone and 10 ng equivalents/mL total radioactivity are achieved within 2.0 hours. The plasma half-life (T½) values for nabilone and total radioactivity of identified and unidentified metabolites are about 2 and 35 hours, respectively. The initial rapid disappearance of radioactivity represents uptake and distribution of nabilone into tissue and the slower phase elimination by metabolism and excretion. The apparent volume of distribution of nabilone is about 12.5 L/kg.

Nabilone exhibits dose linearity within its therapeutic range. Clinical data suggests that the intake of food does not significantly affect either the rate or extent of absorption.

Metabolism: Metabolism of nabilone is extensive and several metabolites have been identified. Precise information concerning the metabolites that may accumulate is not available. The relative activities of the metabolites and the parent drug have not been established. There are at least two metabolic pathways involved in the biotransformation of nabilone. A minor pathway is initiated by the stereospecific enzymatic reduction of the 9-keto moiety of nabilone to produce the isomeric carbinol metabolite. The peak concentrations of nabilone and its carbinol metabolites are comparable, but their combined exposures in plasma do not account for more than 20% of that of total radioactivity. Secondly, a metabolite of nabilone in feces has been identified as a diol formed by reduction of the 9-keto group plus oxidation at the penultimate carbon of the dimethylheptyl side chain. In addition, there is evidence of extensive metabolism of Cesamet by multiple P450 enzyme isoforms. In vitro P450 inhibition studies using human liver microsomes showed that nabilone did not significantly inhibit CYP1A2, 2A6, 2C19, 2D6, and 3A4 (using midazolam and nifedipine as substrates). Nabilone had a weak inhibitory effect on CYP 2E1 and 3A4 (testosterone; IC50> 50 µM) and had a moderate inhibitory effect on CYP2C8 and 2C9 (IC50> 10 µM). However, in clinical use, the very low nabilone plasma concentration is unlikely to interfere with the P450-mediated degradation of co-administered drugs. Chronic oral administration of 1 mg t.i.d. for 14 days to 3 subjects gave no indication there was any significant accumulation of nabilone. Available evidence suggests that one or more of the metabolites has a terminal elimination half-life that exceeds that of nabilone. Consequently, in repeated use, the metabolites may accumulate at concentrations in excess of the parent drug.

Elimination: The route and rate of the elimination of nabilone and its metabolites are similar to those observed with other cannabinoids, including delta-9-THC (dronabinol). When nabilone is administered intravenously, the drug and its metabolites are eliminated mainly in the feces (approximately 67%) and to a lesser extent in the urine (approximately 22%) within 7 days. Of the 67% recovered from the feces, 5% corresponded to the parent compound and 16% to its carbinol metabolite. Following oral administration about 60% of nabilone and its metabolites were recovered in the feces and about 24% in urine. Therefore, it appears that the major excretory pathway is the biliary system.

The effects of age, gender, hepatic dysfunction, and renal insufficiency on the metabolism and elimination of nabilone have not been determined.

Special Populations: The pharmacokinetic profile of Cesamet has not been investigated in either pediatric (see PRECAUTIONS, Pediatric Use) or geriatric patients (see PRECAUTIONS, Geriatric Use).

Clinical Trials

Cesamet was evaluated for its effectiveness and safety in the treatment of nausea and vomiting induced by cancer chemotherapy in patients receiving a wide variety of chemotherapy regimens, including low-dose cisplatin (20 mg/m2) in both placebo-controlled and active controlled (prochlorperazine) trials.

During Cesamet treatment patients reported a higher incidence of adverse effects. The most frequent were drowsiness, vertigo, dry mouth and euphoria. However, most of the adverse effects occurring with Cesamet were of mild to moderate severity (see ADVERSE REACTIONS).

INDICATIONS AND USAGE

Cesamet capsules are indicated for the treatment of the nausea and vomiting associated with cancer chemotherapy in patients who have failed to respond adequately to conventional antiemetic treatments. This restriction is required because a substantial proportion of any group of patients treated with Cesamet can be expected to experience disturbing psychotomimetic reactions not observed with other antiemetic agents.

Because of its potential to alter the mental state, Cesamet is intended for use under circumstances that permit close supervision of the patient by a responsible individual particularly during initial use of Cesamet and during dose adjustments.

Cesamet contains nabilone, which is controlled in Schedule II of the Controlled Substances Act. Schedule II substances have a high potential for abuse. Prescriptions for Cesamet should be limited to the amount necessary for a single cycle of chemotherapy (i.e., a few days).

Cesamet capsules are not intended to be used on as needed basis or as a first antiemetic product prescribed for a patient.

As with all controlled drugs, prescribers should monitor patients receiving nabilone for signs of excessive use, abuse and misuse. Patients who may be at increased risk for substance abuse include those with a personal or family history of substance abuse (including drug or alcohol abuse) or mental illness.

CONTRAINDICATIONS

Cesamet is contraindicated in any patient who has a history of hypersensitivity to any cannabinoid.

WARNINGS

- The effects of Cesamet may persist for a variable and unpredictable period of time following its oral administration. Adverse psychiatric reactions can persist for 48 to 72 hours following cessation of treatment.
- Cesamet has the potential to affect the CNS, which might manifest itself in dizziness, drowsiness, euphoria “high”, ataxia, anxiety, disorientation, depression, hallucinations and psychosis.
- Cesamet can cause tachycardia and orthostatic hypotension.
- Because of individual variation in response and tolerance to the effects of Cesamet, patients should remain under supervision of a responsible adult especially during initial use of Cesamet and during dose adjustments.
- Patients receiving treatment with Cesamet should be specifically warned not to drive, operate machinery, or engage in any hazardous activity while receiving Cesamet.
- Cesamet should not be taken with alcohol, sedatives, hypnotics, or other psychoactive substances because these substances can potentiate the central nervous system effects of nabilone.

PRECAUTIONS

General

The benefit/risk ratio of Cesamet use should be carefully evaluated in patients with the following medical conditions because of individual variation in response and tolerance to the effects of Cesamet.

- Since Cesamet can elevate supine and standing heart rates and cause postural hypotension, it should be used with caution in the elderly, and in patients with hypertension or heart disease.
- Cesamet should also be used with caution in patients with current or previous psychiatric disorders, (including manic depressive illness, depression, and schizophrenia) as the symptoms of these disease states may be unmasked by the use of cannabinoids.
- Cesamet should be used with caution in individuals receiving concomitant therapy with sedatives, hypnotics, or other psychoactive drugs because of the potential for additive or synergistic CNS effects.
- Cesamet should be used with caution in patients with a history of substance abuse, including alcohol abuse or dependence and marijuana use, since Cesamet contains a similar active compound to marijuana.
- The safety aspects of the effects of hepatic and renal impairment have not been investigated.
- Nabilone is purportedly highly bound to plasma proteins and undergoes extensive first pass hepatic metabolism. Those properties have the potential to lead to drug-drug interactions affecting the pharmacokinetics of similar behaving co-administered drugs or of Cesamet itself.
- The effects of QT prolongation potential by Cesamet have not been determined.
- Cesamet should be used with caution in pregnant patients, nursing mothers, or pediatric patients because it has not been studied in these patient populations.

Information for Patients

Persons taking Cesamet should be alerted to the potential for additive central nervous system depression resulting from simultaneous use of Cesamet and alcohol or other central nervous system depressants such as benzodiazepines and barbiturates. This combination should be avoided. Patients receiving treatment with Cesamet should be specifically warned not to drive, operate machinery, or engage in any hazardous activity. Patients using Cesamet should be made aware of possible changes in mood and other adverse behavioral effects of the drug so as to avoid panic in the event of such manifestations. Patients should remain under supervision of a responsible adult while using Cesamet.

Drug Interactions

Potential interactions between Cesamet 2 mg, and diazepam 5 mg; sodium secobarbital 100 mg; alcohol 45 mL (absolute laboratory alcohol); or codeine 65 mg, were evaluated in 15 subjects. Only a single combination was utilized at any one time. The subjects were evaluated according to physiologic (i.e., heart rate and blood pressure), psychometric, psychomotor, and subjective parameters. In this study, as expected, the depressant effects of the combinations were additive. Psychomotor function was particularly impaired with concurrent use of diazepam. Caution must thus be used when administering nabilone in combination with any CNS depressant.

Nabilone is purportedly highly bound to plasma proteins, and therefore, might displace other protein-bound drugs. Therefore, practitioners should monitor patients for a change in dosage requirements when administering nabilone to patients receiving other highly protein-bound drugs. Published reports of drug-drug interactions involving cannabinoids are summarized in the following table.

CONCOMITANT DRUG | CLINICAL EFFECT(S)
Amphetamines, cocaine, other sympathomimetic agents | Additive hypertension, tachycardia, possibly cardiotoxicity
Atropine, scopolamine, antihistamines, other anticholinergic agents | Additive or super-additive tachycardia, drowsiness
Amitriptyline, amoxapine, desipramine, other tricyclic antidepressants | Additive tachycardia, hypertension, drowsiness
Barbiturates, benzodiazepines, ethanol, lithium, opioids, buspirone, antihistamines, muscle relaxants, other CNS depressants | Additive drowsiness and CNS depression
Disulfiram | A reversible hypomanic reaction was reported in a 28 y/o man who smoked marijuana; confirmed by dechallenge and rechallenge
Fluoxetine | A 21 y/o female with depression and bulimia receiving 20 mg/day fluoxetine X 4 wks became hypomanic after smoking marijuana; symptoms resolved after 4 days
Antipyrine, barbiturates | Decreased clearance of these agents, presumably via competitive inhibition of metabolism
Theophylline | Increased theophylline metabolism reported with smoking of marijuana; effect similar to that following smoking tobacco
Opioids | Cross-tolerance and mutual potentiation
Naltrexone | Oral THC effects were enhanced by opioid receptor blockade.
Alcohol | Increase in the positive subjective mood effects of smoked marijuana

Animal Pharmacology and/or Toxicology

Monkeys treated with Cesamet at doses as high as 2 mg/kg/day for a year experienced no significant adverse events. This result contrasts with the findings in a planned 1-year dog study that was prematurely terminated because of deaths associated with convulsions in dogs receiving as little as 0.5 mg/kg/day. The earliest deaths, however, occurred at 56 days in dogs receiving 2 mg/kg/day. The unusual vulnerability of the dog to Cesamet is not understood; it is hypothesized, however, that the explanation lies in the fact that the dog differs markedly from other species in its metabolism of Cesamet.

Carcinogenesis, Mutagenesis, Impairment of Fertility

No long-term studies in animals have been performed to evaluate the carcinogenic potential of nabilone.

Nabilone was not genotoxic in the Ames test, the rat hepatocyte unscheduled DNA synthesis (UDS) test, the Chinese hamster bone marrow cell sister chromatid exchange (SCE) test, the male rat dominant lethal tests nor the rat micronucleus test.

Dietary administration of nabilone up to 4 mg/kg/day (about 6 times the recommended maximum human dose based on body surface area) was found to have no effect on fertility and reproductive performance of male and female rats.

Pregnancy: Teratogenic Effects

Teratology studies conducted in pregnant rats at doses up to 12 mg/kg/day (about 16 times the human dose on a body surface area basis) and in pregnant rabbits at doses up to 3.3 mg/kg/day (about 9 times the human dose on a body surface area basis) did not disclose any evidence for a teratogenic potential of nabilone. However, there was dose related developmental toxicity in both species as evidenced by increases in embryo lethality, fetal resorptions, decreased fetal weights and pregnancy disruptions. In rats, postnatal developmental toxicity was also observed. There are no adequate and well-controlled studies in pregnant women. Because animal studies cannot rule out the possibility of harm, Cesamet should be used during pregnancy only if the potential benefit justifies the potential risk to the fetus.

Nursing Mothers

It is not known whether this drug is excreted in breast milk. Because many drugs including some cannabinoids are excreted in breast milk it is not recommended that Cesamet be given to nursing mothers.

Pediatric Use

Safety and effectiveness have not been established in patients younger than 18 years of age. Caution is recommended in prescribing Cesamet to children because of psychoactive effects.

Geriatric Use

Clinical studies of Cesamet did not include sufficient numbers of subjects aged 65 and over to determine whether they respond differently from younger subjects. In general, dose selection for an elderly patient should be cautious, usually starting at the low end of the dosing range, reflecting the greater frequency of decreased hepatic, renal, or cardiac function, and of concomitant disease or other drug therapy. Cesamet should be used with caution in elderly patients aged 65 and over because they are generally more sensitive to the psychoactive effects of drugs and Cesamet can elevate supine and standing heart rates and cause postural hypotension.

ADVERSE REACTIONS

Commonly Encountered Reactions: During controlled clinical trials of Cesamet, virtually all patients experienced at least one adverse reaction. The most commonly encountered events were drowsiness, vertigo, dry mouth, euphoria (feeling “high”), ataxia, headache, and concentration difficulties.

Comparative Incidence of Reactions: Accurate estimates of the incidence of adverse events associated with the use of any drug are difficult to obtain. Estimates are influenced by factors such as drug dose, detection technique, setting, and physician judgments, among others. Consequently, the tables presented below are presented solely to indicate the relative frequency of adverse events reported in representative controlled clinical studies conducted to evaluate the safety and efficacy of Cesamet under relatively similar conditions of use. The figures cited cannot be used to predict precisely the incidence of untoward events in the course of usual medical practice, in which patient characteristics and other factors may differ from those that prevailed in the clinical trials. These incidence figures also cannot be compared with those obtained from other clinical studies involving related drug products because each group of drug trials is conducted under a different set of conditions.

Finally, it is important to emphasize that these tabulations do not reflect the relative severity and/or clinical importance of the adverse events. A better perspective on the serious adverse events associated with the use of Cesamet is provided in the WARNINGS and PRECAUTIONS sections.

The following tables list in order of decreasing frequency the adverse reactions encountered by a substantial proportion of patients treated with Cesamet participating in representative controlled clinical trials.

Incidence of Adverse Reactions in Placebo-Controlled Studies
 | Nabilone (n=132) |  | Placebo (n=119)
Adverse Event | Patients | Percent | Patients | Percent
Vertigo | 69 | 52 | 3 | 3
Drowsiness | 69 | 52 | 6 | 5
Dry Mouth | 47 | 36 | 2 | 2
Ataxia | 19 | 14 | 0 | 0
Euphoria | 14 | 11 | 1 | 1
Sleep Disturbance | 14 | 11 | 1 | 1
Dysphoria | 12 | 9 | 0 | 0
Headache | 8 | 6 | 0 | 0
Nausea | 5 | 4 | 0 | 0
Disorientation | 3 | 2 | 0 | 0
Depersonalization | 2 | 2 | 1 | 1

Incidence of Adverse Reactions in Active-Controlled Studies
 | Nabilone (n=250) |  | Prochlorperazine (n=232)
Adverse Event | Patients | Percent | Patients | Percent
Drowsiness | 165 | 66 | 108 | 47
Vertigo/Dizziness | 147 | 59 | 53 | 23
Euphoria | 95 | 38 | 12 | 5
Dry Mouth | 54 | 22 | 11 | 5
Depression | 35 | 14 | 37 | 16
Ataxia | 32 | 13 | 4 | 2
Visual Disturbance | 32 | 13 | 9 | 4
Concentration Difficulties | 31 | 12 | 3 | 1
Hypotension | 20 | 8 | 3 | 1
Asthenia | 19 | 8 | 10 | 4
Anorexia | 19 | 8 | 22 | 9
Headache | 18 | 7 | 14 | 6
Sedation | 7 | 3 | 2 | 1
Increased Appetite | 6 | 2 | 2 | 1

Adverse Reactions by Body System—The following list of adverse events is organized by decreasing frequency within body systems for patients treated with Cesamet in controlled clinical trials. All events are listed regardless of causality assessment.

Blood and Hematopoietic—Anemia

Cardiovascular—Orthostatic hypotension, hypotension, tachycardia, syncope, palpitation, flushing, hypertension, arrhythmia, and cerebral vascular accident.

Eye and Ear—Vision disturbance, ear tightness, eye irritation, eye dryness, equilibrium dysfunction, tinnitus, eye disorder, amblyopia, eye swelling, eyelid diseases, pupil dilation, photophobia, and visual field defect.

Gastrointestinal—Dry mouth, nausea, anorexia, vomiting, diarrhea, abdominal pain, constipation, aphthous ulcer, mouth irritation, gastritis, and dyspepsia.

Genitourinary—Increased urination, decreased urination, hot flashes, urinary retention, and frequency of micturition.

Infection—Bacterial infection

Metabolic and Endocrine—Thirst

Musculoskeletal—Muscle pain, back pain, neck pain, joint pain, and unspecified pain.

Nervous System—Drowsiness, vertigo, ataxia, decreased concentration, sedation, hallucinations, paresthesia, tremor, memory disturbance, perception disturbance, convulsions, dystonia, numbness, and akathisia.

Psychiatric—Euphoria (feeling “high”), sleep disturbance, depression, confusion, disorientation, anxiety, depersonalization syndrome, speech disorder, abnormal dreams, insomnia, mood swings, inebriated feeling, toxic psychosis, paranoia, apathy, thought disorder, withdrawal, panic disorder, phobic neurosis, emotional disorder, and hyperactivity.

Respiratory—Dyspnea, pharyngitis, nasal congestion, sinus headache, thick tongue, dry throat, dry nose, wheezing, nosebleed, cough, voice change, and chest pain.

Skin and Appendages—Anhidrosis, photosensitivity, pruritus, rash, and allergic reactions.

Miscellaneous and Ill-Defined Conditions—Headache, fatigue, lightheadedness, coordination disturbance, asthesia, dysphoria, dizziness, taste change, excessive appetite, chills, excessive sweating, nervousness, malaise, postural dizziness, twitch, irritability, fever, inhibited walking, unconsciousness, hypotonia, and impaired urination.

Postmarketing Adverse Reactions—Cesamet has been marketed internationally since 1982. The following adverse reactions listed in order of decreasing frequency by body system have been reported since Cesamet has been marketed. All events are listed regardless of causality assessment.

Blood and Hematopoietic—Leukopenia

Cardiovascular—Hypotension and tachycardia

Eye and Ear—Visual disturbances

Gastrointestinal—Dry mouth, nausea, vomiting, and constipation

Nervous System—Hallucinations, CNS depression, CNS stimulation, ataxia, stupor, vertigo, convulsion, and circumoral paresthesia

Psychiatric—Somnolence, confusion, euphoria, depression, dysphoria, depersonalization, anxiety, psychosis, and emotional lability

Miscellaneous and Ill-Defined Conditions—Dizziness, headache, insomnia, abnormal thinking, chest pain, lack of effect, and face edema

To report SUSPECTED ADVERSE REACTIONS, contact Bausch Health US, LLC at 1-800-321-4576 or FDA at 1-800-FDA-1088 or www.fda.gov/medwatch.

DRUG ABUSE AND DEPENDENCE

Controlled Substance—Cesamet, a synthetic cannabinoid pharmacologically related to Cannabis sativa L. (Marijuana; (delta-9-THC) is a highly abusable substance. Cesamet is controlled under Schedule II (CII) of the Controlled Substances Act. Prescriptions for Cesamet should be limited to the amount necessary for a single cycle of chemotherapy (i.e., a few days). Cesamet may produce subjective side effects which may be interpreted as a euphoria or marijuana-like “high” at therapeutic doses.

It is not known what proportion of individuals exposed chronically to Cesamet or other cannabinoids will develop either psychological or physical dependence. Long term use of these compounds has, however, been associated with disorders of motivation, judgment, and cognition. It is not clear, though, if this is a manifestation of the underlying personalities of chronic users of this class of drugs or if cannabinoids are directly responsible for these effects. An abstinence syndrome has been reported following discontinuation of delta-9-THC at high doses of 200 mg per day for 12 to 16 consecutive days. The acute phase was characterized by psychic distress, insomnia, and signs of autonomic hyperactivity (sweating, rhinorrhea, loose stools, hiccups). A protracted abstinence phase may have occurred in subjects who reported sleep disturbances for several weeks after delta-9-THC discontinuation.

Abuse—Cesamet may produce subjective side effects that may be interpreted as a euphoria or marijuana-like “high” at therapeutic doses. Cesamet was shown to be qualitatively and quantitatively similar to delta-9-THC in the production of cannabis-like effects, thus demonstrating that Cesamet has a high potential for abuse.

Preclinical studies performed in both dogs and monkeys demonstrated that Cesamet was cannabinoid-like. As with delta-9-THC, tolerance develops rapidly to the pharmacological effects in both the dog and the monkey. Cross-tolerance between Cesamet and delta-9-THC was demonstrated in the monkey.

Dependence—The physical dependence capacity of Cesamet is unknown at this time. Patients who participated in clinical trials of up to 5 days’ duration evidenced no withdrawal symptoms on cessation of dosing.

OVERDOSAGE

Signs and Symptoms—Signs and symptoms of overdosage are an extension of the psychotomimetic and physiologic effects of Cesamet.

Treatment—To obtain up-to-date information about the treatment of overdose, a good resource is your certified Regional Poison Control Center. Telephone numbers of certified poison control centers are listed in the Physicians’ Desk Reference (PDR). In managing overdosage, consider the possibility of multiple drug overdoses, interaction among drugs, and unusual drug kinetics in your patient.

Overdosage may be considered to have occurred, even at prescribed dosages, if disturbing psychiatric symptoms are present. In these cases, the patient should be observed in a quiet environment and supportive measures, including reassurance, should be used. Subsequent doses should be withheld until patients have returned to their baseline mental status; routine dosing may then be resumed if clinically indicated. In such instances, a lower initiating dose is suggested. In controlled clinical trials, alterations in mental status related to the use of Cesamet resolved within 72 hours without specific medical therapy.

In overdose settings, attention should be paid to vital signs, since both hypertension and hypotension have been known to occur; tachycardia and orthostatic hypotension were most commonly reported.

No cases of overdosage with more than 10 mg/day of nabilone were reported during clinical trials. Signs and symptoms that would be expected to occur in large overdose situations are psychotic episodes, including hallucinations, anxiety reactions, respiratory depression, and coma.

If psychotic episodes occur, the patient should be managed conservatively, if possible. For moderate psychotic episodes and anxiety reactions, verbal support and comforting may be sufficient. In more severe cases, antipsychotic drugs may be useful; however, the utility of antipsychotic drugs in cannabinoid psychosis has not been systematically evaluated. Support for their use is drawn from limited experience using antipsychotic agents to manage cannabis overdoses. Because of the potential for drug-drug interactions (e.g., additive CNS depressant effects due to nabilone and chlorpromazine), such patients should be closely monitored.

Protect the patient’s airway and support ventilation and perfusion. Meticulously monitor and maintain, within acceptable limits, the patient’s vital signs, blood gases, serum electrolytes, as well as other laboratory values and physical assessments. Absorption of drugs from the gastrointestinal tract may be decreased by giving activated charcoal, which, in many cases, is more effective than emesis or lavage; consider charcoal instead of or in addition to gastric emptying. Repeated doses of charcoal over time may hasten elimination of some drugs that have been absorbed. Safeguard the patient’s airway when employing gastric emptying or charcoal.

The use of forced diuresis, peritoneal dialysis, hemodialysis, charcoal hemoperfusion, or cholestyramine has not been reported. In the presence of normal renal function, most of a dose of nabilone is eliminated through the biliary system.

Treatment for respiratory depression and comatose state consists in symptomatic and supportive therapy. Particular attention should be paid to the occurrence of hypothermia. If the patient becomes hypotensive, consider fluids, inotropes, and/or vasopressors.

The estimated oral median lethal dose in female mice is between 1,000 and 2,000 mg/kg; in the female rat, it is greater than 2,000 mg/kg (see CLINICAL PHARMACOLOGY).

DOSAGE AND ADMINISTRATION

The usual adult dosage is 1 or 2 mg 2 times a day. On the day of chemotherapy, the initial dose should be given 1 to 3 hours before the chemotherapeutic agent is administered. To minimize side effects, it is recommended that the lower starting dose be used and that the dose be increased as necessary. A dose of 1 or 2 mg the night before may be useful. The maximum recommended daily dose is 6 mg given in divided doses 3 times a day.

Cesamet may be administered 2 or 3 times a day during the entire course of each cycle of chemotherapy and, if needed, for 48 hours after the last dose of each cycle of chemotherapy.

HOW SUPPLIED

Cesamet® capsules (blue and white): 1 mg (bottles of 50 capsules) NDC 0187-1231-50. Capsules are imprinted with ICN on the blue cap and a four-digit code (3101) on the white body. Store at controlled room temperature 25°C (77°F); excursions permitted to 15° to 30°C (59° to 86°F) [see USP Controlled Room Temperature].

Distributed by:

Bausch Health US, LLC
Bridgewater, NJ 08807 USA

Manufactured by:
Bausch Health Companies Inc.
Laval, Quebec H7L 4A8, Canada

Cesamet is a trademark of Bausch Health Companies Inc. or its affiliates.

© 2021 Bausch Health Companies Inc. or its affiliates

9754700 Rev. 02/2021

PACKAGE/LABEL PRINCIPAL DISPLAY PANEL

NDC 0187-1231-50
Rx Only

Cesamet® CII
(nabilone)
capsules
1 mg

50 Capsules

Each capsule
contains 1 mg
nabilone

BAUSCH Health